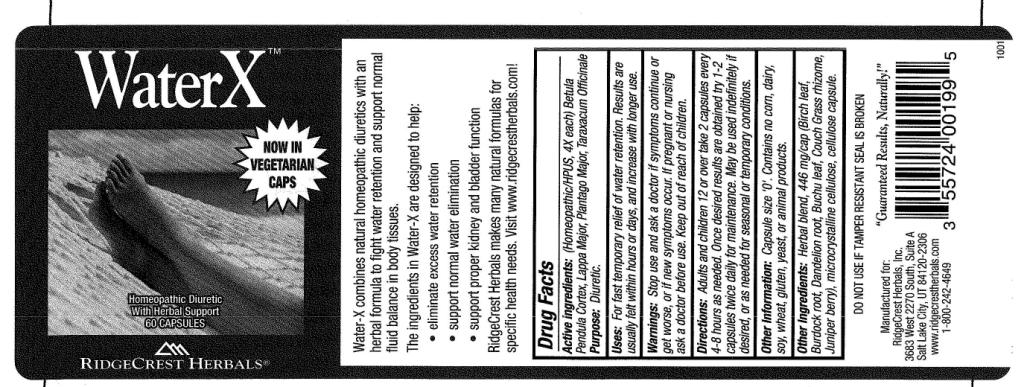 DRUG LABEL: Water 
NDC: 57520-0595 | Form: CAPSULE
Manufacturer: Apotheca Company
Category: homeopathic | Type: HUMAN OTC DRUG LABEL
Date: 20110125

ACTIVE INGREDIENTS: BETULA PENDULA BARK 4 [hp_X]/1 g; ARCTIUM LAPPA ROOT 4 [hp_X]/1 g; PLANTAGO MAJOR 4 [hp_X]/1 g; TARAXACUM OFFICINALE 4 [hp_X]/1 g
INACTIVE INGREDIENTS: CELLULOSE, MICROCRYSTALLINE; BETULA PUBESCENS LEAF; ARCTIUM LAPPA ROOT; TARAXACUM OFFICINALE ROOT; AGATHOSMA BETULINA LEAF; ELYMUS REPENS ROOT; JUNIPERUS COMMUNIS FRUIT; POWDERED CELLULOSE

Water X

ACTIVE INGREDIENT

ACTIVE INGREDIENTS: Betula pendula, cortex 4X, Lappa major 4X, Plantago major 4X, Taraxacum officinale 4X.

PURPOSE

USES: For fast temporary relief of water retention. Results are usually felt within hours or days, and increase with longer use.

WARNINGS

WARNINGS: Stop use and ask a doctor if symptoms continue or get worse, or if new symptoms occur.

If pregnant or nursing ask a doctor before use.

Keep out of reach of children.

DOSAGE AND ADMINISTRATION

DIRECTIONS: Adults and children 12 or over take 2 capsules every 4-8 hours as needed. Once desired results are obtained try 1-2 capsules twice daily for maintenance. May be used indefinitely if desired, or as needed for seasonal or temporary conditions.

INACTIVE INGREDIENT

OTHER INGREDIENTS: Birch leaf. Burdock root, Dandelion root, Buchu leaf, Couch grass rhizome, Juniper berry, Microcrystalline cellulose, cellulose capsule.

KEEP OUT OF REACH OF CHILDREN.

INDICATIONS AND USAGE

USES: For fast temporary relief of water retention. Results are usually felt within hours or days, and increase with longer use.

QUESTIONS

Manufactured for:

RidgeCrest Herbals, Inc.

3683 West 2270 South, Suite A

Salt Lake City, UT 84120-2306

www.ridgecrestherbals.com

1-800-242-4649

PACKAGE LABEL

Water X

NOW IN VEGETARIAN CAPS

HOMEOPATHIC DIURETIC

WITH HERBAL SUPPORT

60 CAPSULES

RidgeCrest Herbals